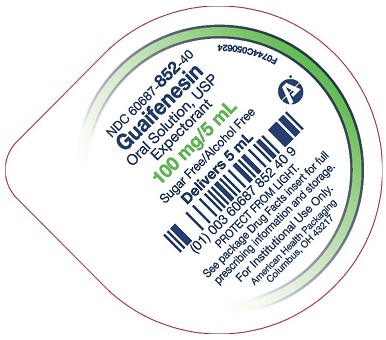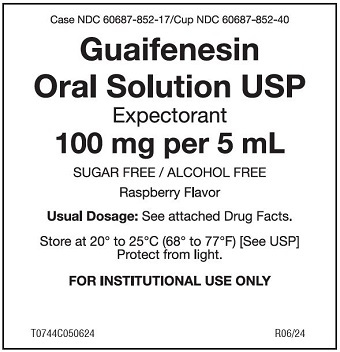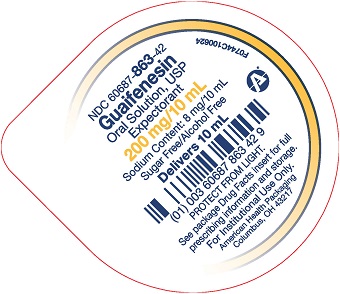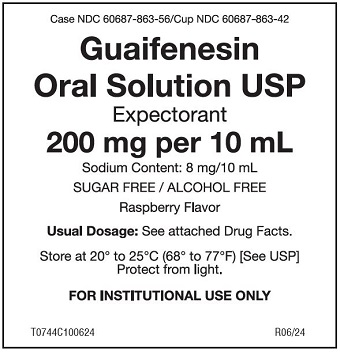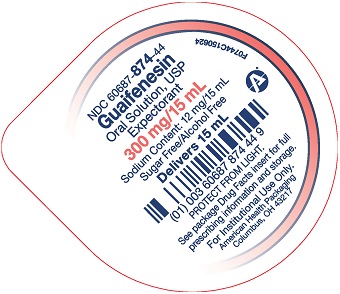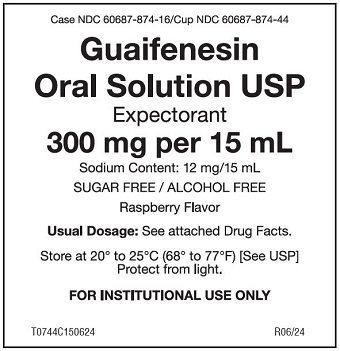 DRUG LABEL: Guaifenesin
NDC: 60687-852 | Form: SOLUTION
Manufacturer: American Health Packaging
Category: otc | Type: HUMAN OTC DRUG LABEL
Date: 20241017

ACTIVE INGREDIENTS: GUAIFENESIN 100 mg/5 mL
INACTIVE INGREDIENTS: ACESULFAME POTASSIUM; FD&C GREEN NO. 3; FD&C RED NO. 40; HYDROXYETHYL CELLULOSE, UNSPECIFIED; WATER; SODIUM BENZOATE; SODIUM CITRATE, UNSPECIFIED FORM; ANHYDROUS CITRIC ACID

Guaifenesin Oral Solution USP
Drug Facts

Expectorant
SUGAR FREE / ALCOHOL FREE

Active ingredient

- (in each 5 mL Cup) Guaifenesin 100 mg
- (in each 10 mL Cup) Guaifenesin 200 mg
- (in each 15 mL Cup) Guaifenesin 300 mg

Purpose

Expectorant

Uses

- helps loosen phlegm (mucus) and thin bronchial secretions to make coughs more productive

Warnings

Ask a doctor before use if you have

- cough that occurs with too much phlegm (mucus)
- cough that lasts or is chronic such as occurs with smoking, asthma, chronic bronchitis, or emphysema

Stop use and ask a doctor if

- cough lasts more than 7 days, comes back, or is accompanied by fever, rash, or persistent headache. These could be signs of a serious condition.
- you are hypersensitive to any of the ingredients.

If pregnant or breast-feeding,

ask a health professional before use.

Keep out of reach of children.

In case of overdose, get medical help or contact a Poison Control Center right away .

Directions

Follow dosage below or use as directed by a physician.

- do not take more than 6 doses in any 24-hour period.

Age (yr) | Dose (ml)
adults and children 12 years and over | 10 to 20 ml (2 to 4 teaspoonfuls) every 4 hours
children 6 years to under 12 years | 5 to 10 ml (1 to 2 teaspoonfuls) every 4 hours
children 2 years to under 6 years | 2.5 to 5 ml (1 /2 to 1 teaspoonful) every 4 hours
children under 2 years | consult a physician

Other Information

- Each 5 ml contains: sodium 4 mg.
- Each 10 ml contains: sodium 8 mg.
- Each 15 ml contains: sodium 12 mg.
- Store at controlled room temperature between 20° to 25°C (68° to 77°F) [see USP]. Protect from light.
- DO NOT USE IF SEAL IS BROKEN.
- Guaifenesin Oral Solution is a red, raspberry flavored solution and is available in the following dosage forms:
  5 ml unit-dose cups: 100 cups (10 x 10) NDC 60687-852-17
  10 ml unit-dose cups: 100 cups (10 x 10) NDC 60687-863-56
  15 ml unit-dose cups: 100 cups (10 x 10) NDC 60687-874-16

Inactive Ingredients

Acesulfame K, citric acid, FD&C Green No. 3, FD&C Red No. 40, flavoring, hydroxyethylcellulose, purified water, sodium benzoate, and sodium citrate.

Questions or comments?

Call 1-800-845-8210

Generic Section

Professional Note: Guaifenesin has been shown to produce a color interference with certain clinical laboratory determinations of 5-hydroxyindoleacetic acid (5-HIAA) and vanillylmandelic acid (VMA).

Distributed by:
American Health Packaging
Columbus, OH 43217

R0624

Package/Label Principal Display Panel – 100 mg per 5 mL – Label

Case NDC 60687- 852-17/Cup NDC 60687- 852-40

Guaifenesin
Oral Solution USP
Expectorant

100 mg per 5 ml

SUGAR FREE / ALCOHOL FREE
Raspberry Flavor

Usual Dosage: See attached Drug Facts.

Store at 20° to 25°C (68° to 77°F) [See USP]
Protect from light.

FOR INSTITUTIONAL USE ONLY

T0744C050624 R0624

Package/Label Principal Display Panel – 100 mg per 5 mL – Cup Lid

NDC 60687- 852-40

Guaifenesin
Oral Solution, USP
Expectorant

100 mg per 5 ml

Sugar Free/Alcohol Free
Delivers 5 mL

PROTECT FROM LIGHT.

See package Drug Facts insert for full
prescribing information and storage.

For Institutional Use Only.

American Health Packaging
Columbus, OH 43217

F0744C050624

Package/Label Principal Display Panel – 200 mg per 10 mL – Label

Case NDC 60687- 863-56/Cup NDC 60687- 863-42

Guaifenesin
Oral Solution USP
Expectorant

200 mg per 10 ml

Sodium Content: 8 mg/10 ml
SUGAR FREE / ALCOHOL FREE
Raspberry Flavor

Usual Dosage: See attached Drug Facts.

Store at 20° to 25°C (68° to 77°F) [See USP]
Protect from light.

FOR INSTITUTIONAL USE ONLY

T0744C100624 R0624

Package/Label Principal Display Panel – 200 mg per 10 mL – Cup Lid

NDC 60687- 863-42

Guaifenesin
Oral Solution, USP
Expectorant

200 mg per 10 ml

Sodium Content: 8 mg/10 ml
Sugar Free/Alcohol Free
Delivers 10 mL

PROTECT FROM LIGHT.

See package Drug Facts insert for full
prescribing information and storage.

For Institutional Use Only.

American Health Packaging
Columbus, OH 43217

F0744C100624

Package/Label Principal Display Panel – 300 mg per 15 mL – Label

Case NDC 60687- 874-16/Cup NDC 60687- 874-44

Guaifenesin
Oral Solution USP
Expectorant

300 mg per 15 ml

Sodium Content: 12 mg/15 ml
SUGAR FREE / ALCOHOL FREE
Raspberry Flavor

Usual Dosage: See attached Drug Facts.

Store at 20° to 25°C (68° to 77°F) [See USP]
Protect from light.

FOR INSTITUTIONAL USE ONLY

T0744C150624 R0624

Package/Label Principal Display Panel – 300 mg per 15 mL – Cup Lid

NDC 60687- 874-44

Guaifenesin
Oral Solution, USP
Expectorant

300 mg per 15 ml

Sodium Content: 12 mg/15 ml
Sugar Free/Alcohol Free
Delivers 15 mL

PROTECT FROM LIGHT.

See package Drug Facts insert for full
prescribing information and storage.

For Institutional Use Only.

American Health Packaging
Columbus, OH 43217

F0744C150624